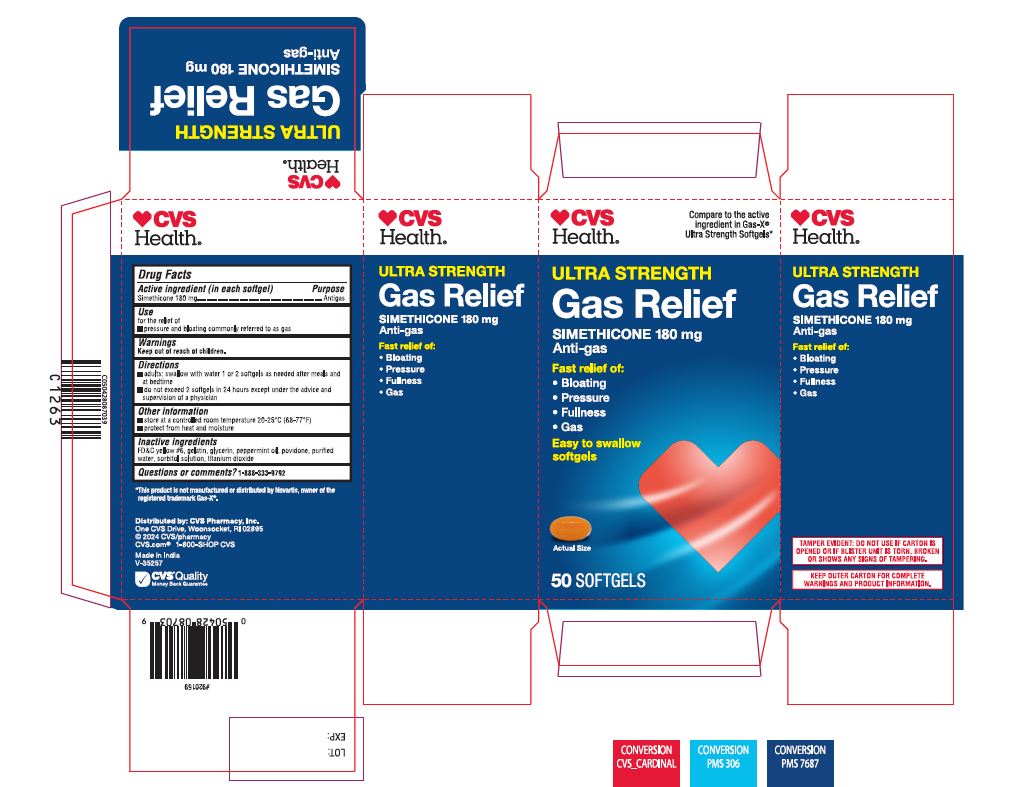 DRUG LABEL: CVS Health Ultra Strength Gas Relief
NDC: 51316-108 | Form: CAPSULE, LIQUID FILLED
Manufacturer: CVS Pharmacy
Category: otc | Type: HUMAN OTC DRUG LABEL
Date: 20241218

ACTIVE INGREDIENTS: DIMETHICONE 180 mg/1 1
INACTIVE INGREDIENTS: FD&C YELLOW NO. 6; GELATIN; GLYCERIN; PEPPERMINT OIL; POVIDONE; WATER; SORBITOL SOLUTION; TITANIUM DIOXIDE

CVS Health Ultra Strength Gas Relief